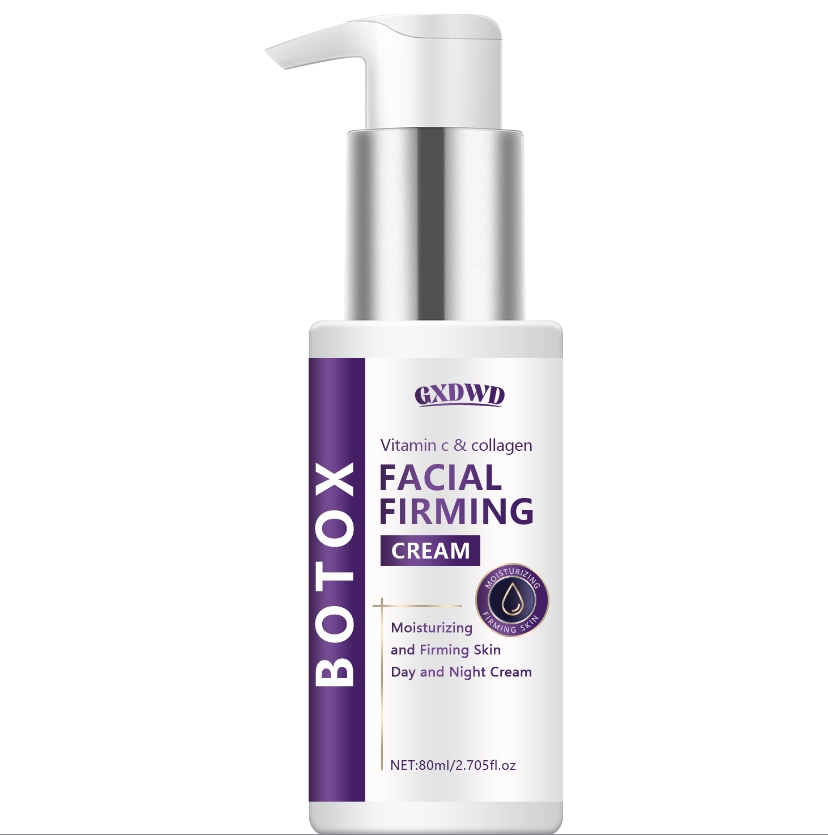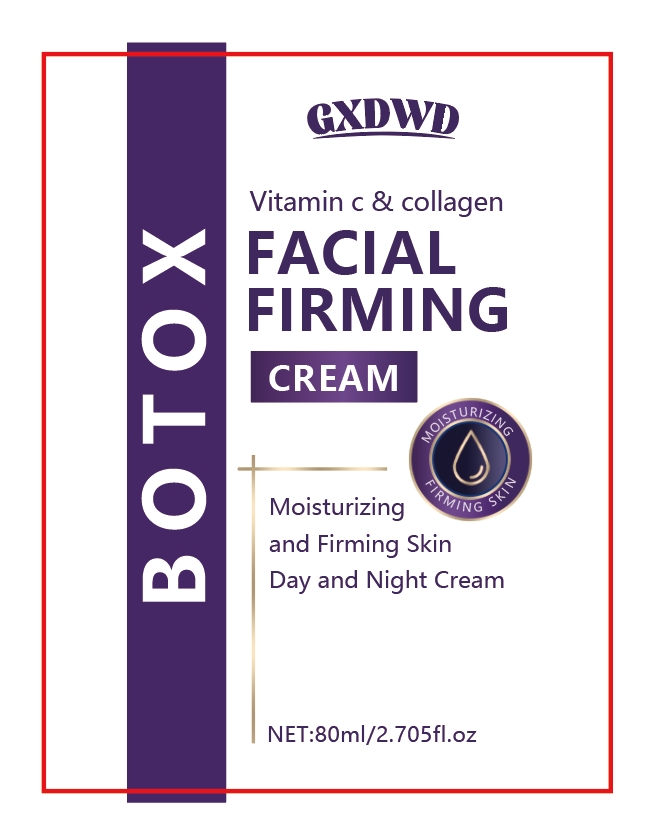 DRUG LABEL: facial essence
NDC: 84025-169 | Form: CREAM
Manufacturer: Guangzhou Yanxi Biotechnology Co.. Ltd
Category: otc | Type: HUMAN OTC DRUG LABEL
Date: 20240827

ACTIVE INGREDIENTS: NIACINAMIDE 5 mg/80 mL; CETEARYL OLIVATE 3 mg/80 mL
INACTIVE INGREDIENTS: WATER

DOSAGE AND ADMINISTRATION

Cream for moisturizing and maintaining facial skin

WARNINGS

Keep out of children

INACTIVE INGREDIENT

AQUA

INDICATIONS AND USAGE

For daily skin care

keep out of children

PURPOSE

Effectively tightens and moisturizes facial skin